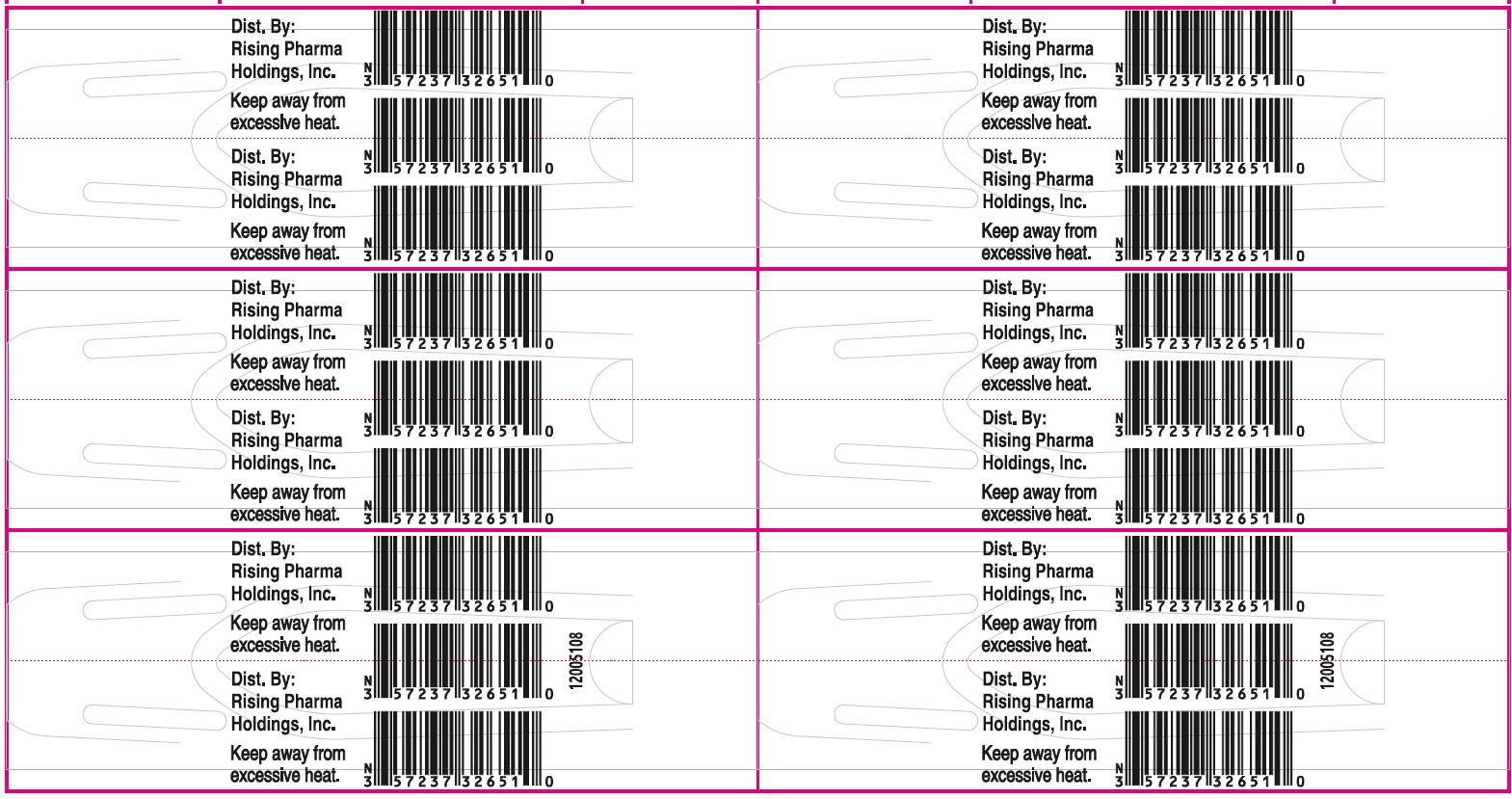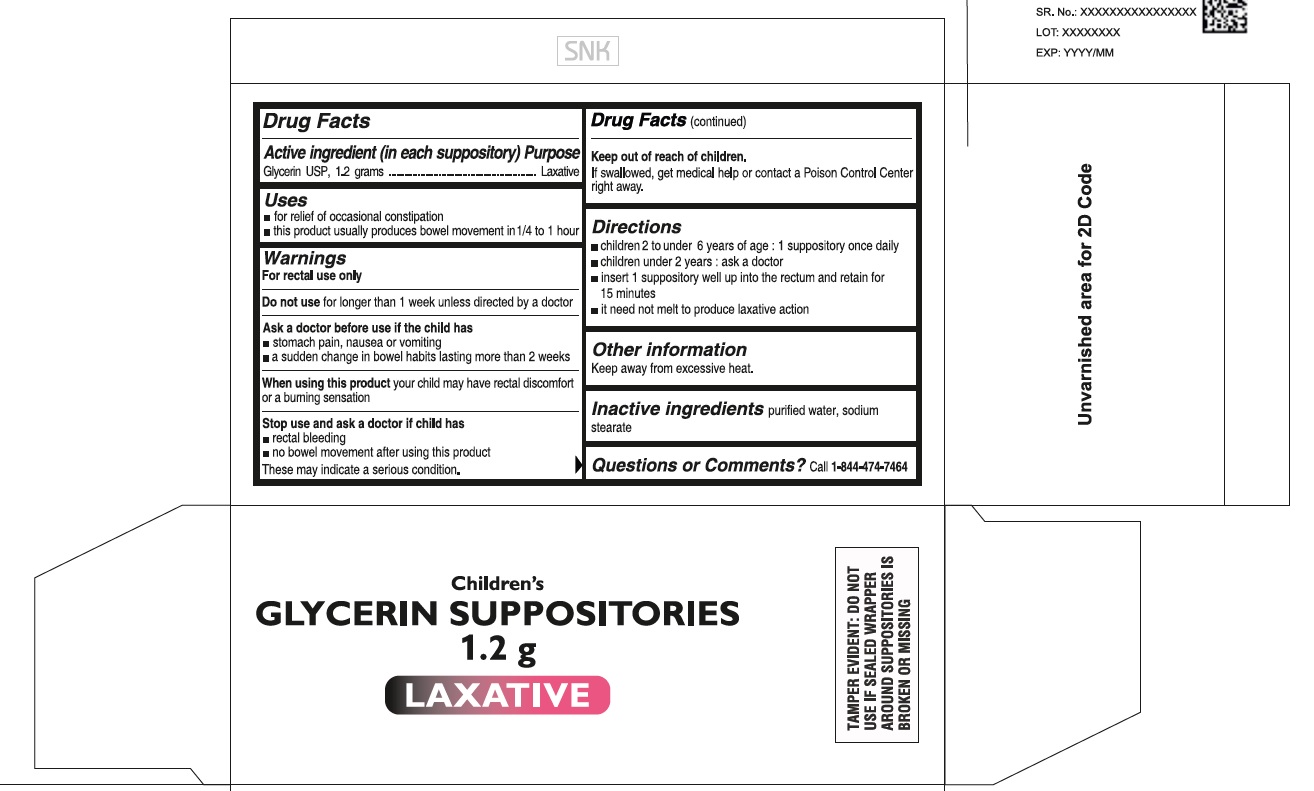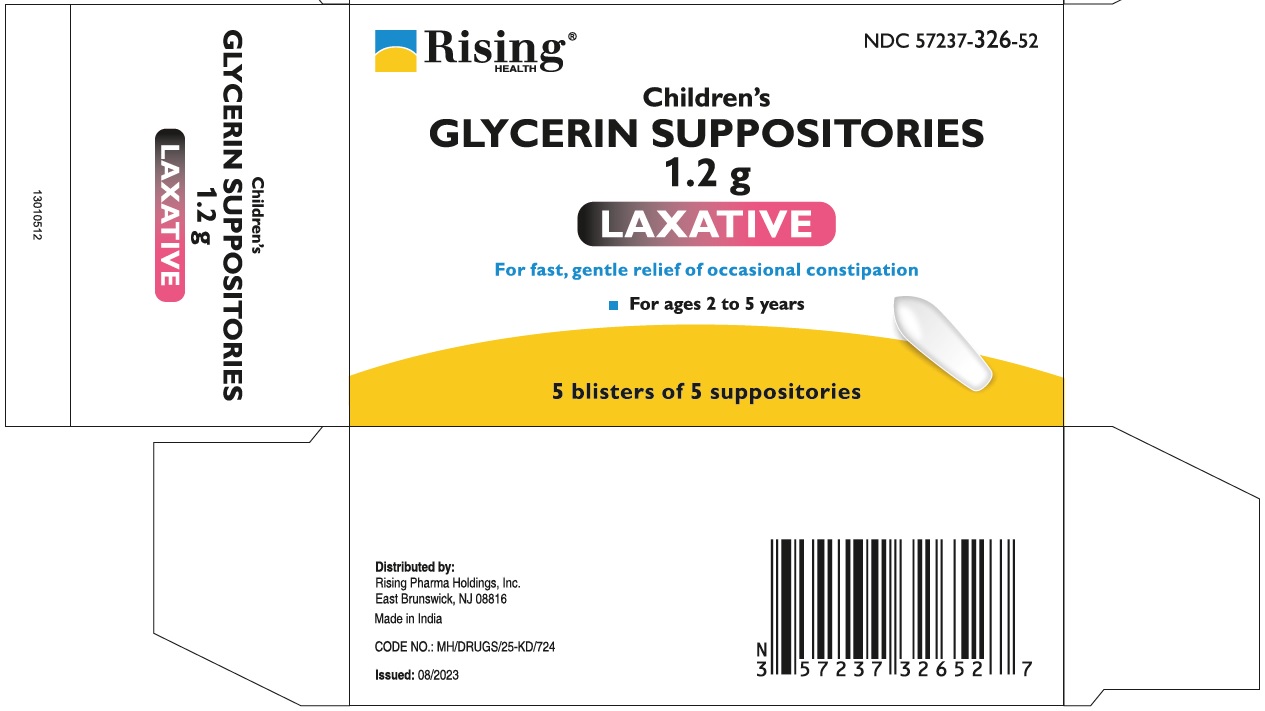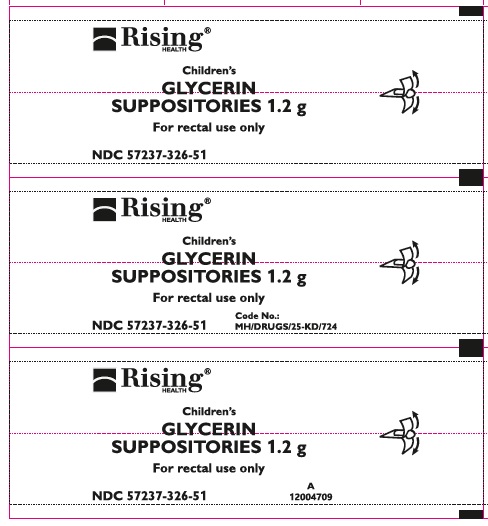 DRUG LABEL: Glycerin
NDC: 57237-326 | Form: SUPPOSITORY
Manufacturer: Rising Pharma Holdings, Inc.
Category: otc | Type: HUMAN OTC DRUG LABEL
Date: 20250908

ACTIVE INGREDIENTS: GLYCERIN 1.2 g/1 1
INACTIVE INGREDIENTS: WATER; SODIUM STEARATE

Children’s Glycerin Suppositories 1.2 g

Drug Facts

Active ingredient (in each suppository)

Glycerin USP, 1.2 grams

Purpose

Laxative

Uses

- for relief of occasional constipation
- this product usually produces bowel movement in 1/4 to 1 hour

Warnings

For rectal use only

Do not use for longer than one week unless directed by a doctor

Ask a doctor before use if the child has

- stomach pain, nausea or vomiting
- a sudden change in bowel habits lasting more than 2 weeks

When using this product your child may have rectal discomfort or a burning sensation

Stop use and ask a doctor if child has

- rectal bleeding
- no bowel movement after using this product

These may indicate a serious condition.

Keep out of reach of children.

If swallowed, get medical help or contact a Poison Control Center right away.

Directions

- children 2 to under 6 years of age : 1 suppository once daily
- children under 2 years : ask a doctor
- insert 1 suppository well up into the rectum and retain for 15 minutes
- it need not melt to produce laxative action

Other information

keep away from excessive heat.

Inactive ingredients purified water, sodium stearate

Questions or Comments? Call 1-844-474-7464

TAMPER EVIDENT: DO NOT USE IF SEALED WRAPPER AROUND SUPPOSITORIES IS BROKEN OR MISSING

Distributed by:
Rising Pharma Holdings, Inc.
East Brunswick, NJ 08816

Made in India

CODE NO.: MH/DRUGS/25-KD/724

Issued: 08/2023

PACKAGE LABEL

NDC 57237-326-52 (5 blisters of 5 suppositories)

Children's Glycerin Suppositories 1.2 g

LAXATIVE

For fast, gentle relief of occasional constipation

For ages 2 to 5 years

NDC 57237-326-51 (5 suppositories in 1 blister pack)

Front Foil

Back Foil